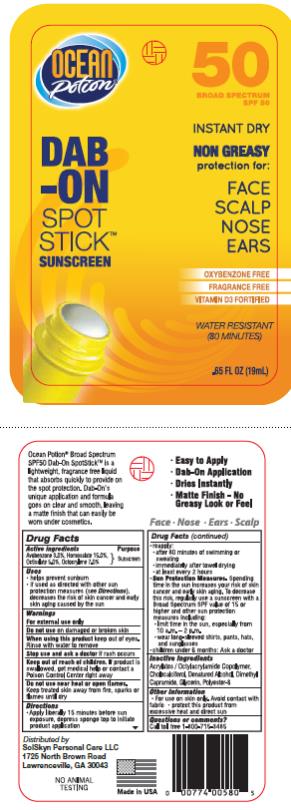 DRUG LABEL: Face Potion
NDC: 70281-204 | Form: LOTION
Manufacturer: SolSkyn Personal Care LLC
Category: otc | Type: HUMAN OTC DRUG LABEL
Date: 20180215

ACTIVE INGREDIENTS: AVOBENZONE 3 g/100 g; HOMOSALATE 15 g/100 g; OCTISALATE 5 g/100 g; OCTOCRYLENE 7 g/100 g
INACTIVE INGREDIENTS: CHOLECALCIFEROL; ALCOHOL; DIMETHYL CAPRAMIDE; GLYCERIN; POLYESTER-8 (1400 MW, CYANODIPHENYLPROPENOYL CAPPED)

OP SPF 50 Dab on Stick

OP Dab-On Spot stick SPF 50

Drug Facts

Active Ingredients:

Avobenzone 2.5%

Active Ingredients:

Homosalate 15.0%

Active Ingredients:

Octisalate 5.0%

Active Ingredients:

Oxybenzone 6.0%

Purpose

Sunscreen

Uses:

• Helps prevent sunburn

• If used as directed with other sun protection measures (see Directions), decreases the risk of skin cancer and early skin aging caused by the sun

Warnings:

• For external use only.

• Do not use

on damaged or broken skin

• Stop use and ask a doctor

if rash or irritation develops.

• When using this product

keep out of eyes. Rinse with water to remove.

• Keep out of reach of children.

If accidentally swallowed, contact a Poison Control Center right away.

• Do not use

near heat or open flames. Keep treated skin away from fire, sparks or flames until dry.

Directions:

• Apply liberally 15 minutes before sun exposure, depress sponge top to initial product application

• Re-apply:

• after 80 minutes of swimming or sweating

• immediately after towel drying

• at least every two hours.

• Sun Protection Measures. Spending time in the sun increases your risk of skin cancer and early skin aging. To decrease this risk, regularly use a sunscreen with a Broad Spectrum SPF value of 15 or higher and other sun protection measures including:

• limit time in the sun, especially from 10 a.m.-2 p.m.

• wear long-sleeved shirts, pants, hats and sunglasses

• Children under 6 months: ask a doctor.

Inactive Ingredients

Acrylates/Octylacrylamide Copolymer, Cholecalciferol, Denatured Alcohol, Dimethyl Capramide, Glycerin, Polyester-8

Other Information

• for use on skin only. Avoid contact with fabric - protect this product from excessive heat and direct sun.

Questions or comments?

Call toll free 1-800-715-3485

PRINCIPAL DISPLAY PANEL

DAB- ON
Spot Stick Sunscreen
50 SPF
65 FL OZ (19mL)